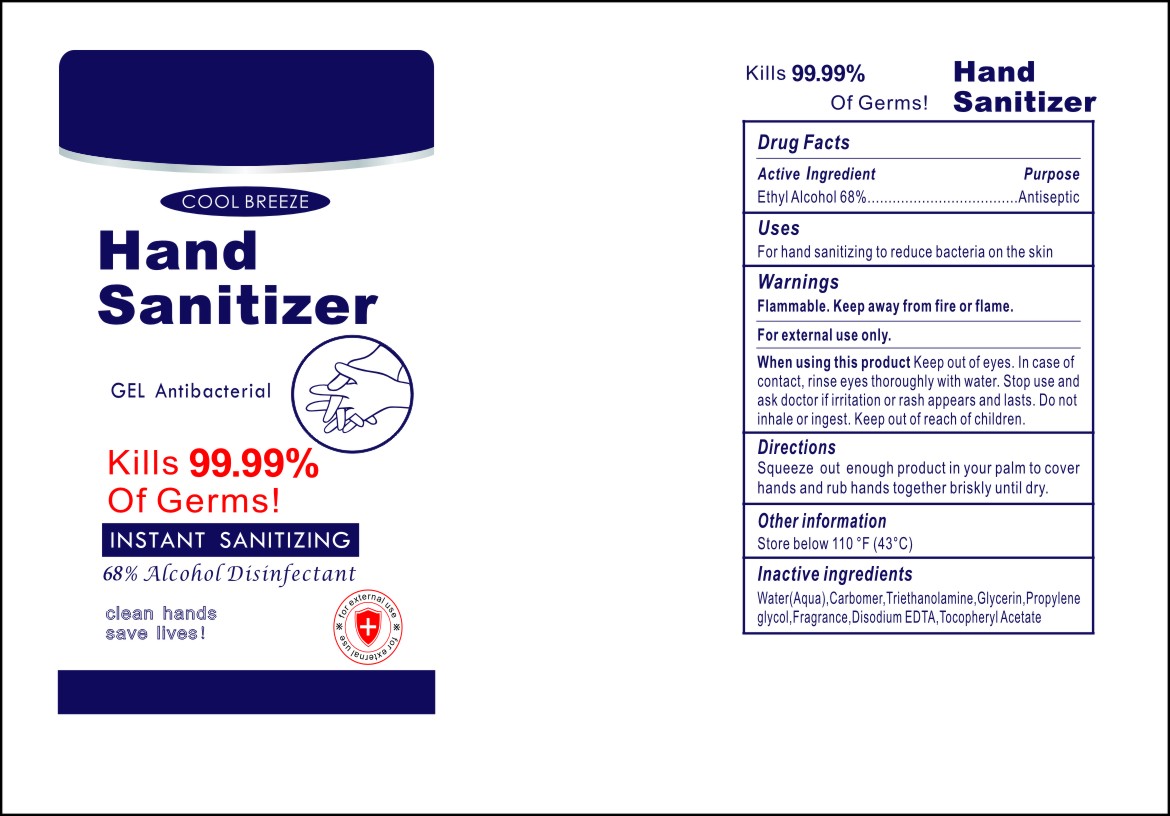 DRUG LABEL: Hand Sanitizer
NDC: 75613-101 | Form: GEL
Manufacturer: Ningbo Lanzi Cosmetic Technology Co., Ltd
Category: otc | Type: HUMAN OTC DRUG LABEL
Date: 20220303

ACTIVE INGREDIENTS: ALCOHOL 68 g/100 mL
INACTIVE INGREDIENTS: EDETATE DISODIUM ANHYDROUS; .ALPHA.-TOCOPHEROL ACETATE, D-; GLYCERIN; WATER; CARBOMER HOMOPOLYMER, UNSPECIFIED TYPE; CLOVE; TROLAMINE; PROPYLENE GLYCOL

Lanzi, Hand Sanitizer, 68% Ethyl Alcohol, Gel, xx mL

Active Ingredient(s)

Ethyl Alcohol 68% w/w. Purpose: Antiseptic

Purpose

Antiseptic

Use

For hand sanitizing to reduce bacteria on the skin.

Warnings

Flammable.

Keep away from fire or flame.

For external use only.

Do not inhale or ingest.

Do not use

Do not inhale or ingest.

When using this product Keep out of eyes.

In case of contact, rinse eyes thoroughly with water.

Stop use and ask a doctor if irritation or rash appears or lasts.

Keep out of reach of children. If swallowed, get medical help or contact a Poison Control Center right away.

Directions

Squeeze out enough product in your palm to cover hands and rub hands together briskly until dry.

Other information

Store below 110℉ (43℃).

Inactive ingredients

Ethyl Alcohol, Glycerin, Propylene Glycol, Triethanolamine, Carbomer, Fragrance, Disodium EDTA, Tocopheryl Acetate, Deionized Water.